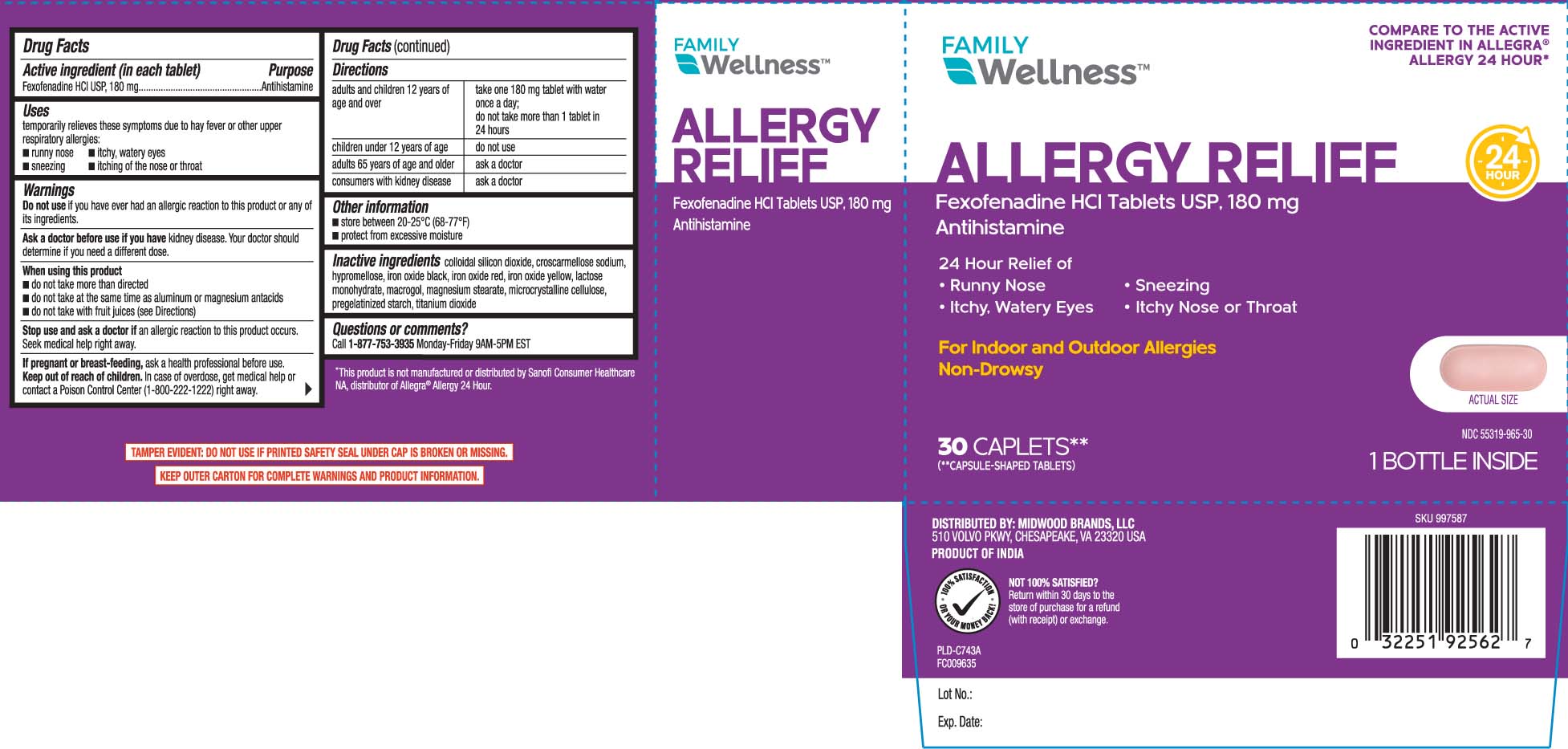 DRUG LABEL: Allergy Relief
NDC: 55319-965 | Form: TABLET
Manufacturer: Family Dollar (FAMILY WELLNESS)
Category: otc | Type: HUMAN OTC DRUG LABEL
Date: 20251003

ACTIVE INGREDIENTS: FEXOFENADINE HYDROCHLORIDE 180 mg/1 1
INACTIVE INGREDIENTS: SILICON DIOXIDE; CROSCARMELLOSE SODIUM; HYPROMELLOSES; FERRIC OXIDE RED; FERRIC OXIDE YELLOW; LACTOSE MONOHYDRATE; POLYETHYLENE GLYCOL, UNSPECIFIED; TITANIUM DIOXIDE; FERROSOFERRIC OXIDE; STARCH, CORN; MAGNESIUM STEARATE

DRUG FACTS

Active ingredient (in each tablet)

Fexofenadine HCl USP 180 mg

Purpose

Antihistamine

Uses

temporarily relieves these symptoms due to hay fever or other upper respiratory allergies:

- runny nose
- itchy, watery eyes
- sneezing
- itching of the nose or throat

Warnings

Do not use

if you have ever had an allergic reaction to this product or any of its ingredients.

Ask a doctor before use if you have

kidney disease. Your doctor should determine if you need a different dose.

When using this product

- do not take more than directed
- do not take at the same time as aluminum or magnesium antacids
- do not take with fruit juices (see Directions)

Stop use and ask a doctor if

an allergic reaction to this product occurs. Seek medical help right away.

If pregnant or breast-feeding,

ask a health professional before use.

Keep out of reach of children.

In case of overdose, get medical help or contact a Poison Control Center (1-800-222-1222) right away.

Directions

adults and children 12 years of age and over | take one 180 mg tablet with water once a day;; do not take more than 1 tablet in 24 hours
children under 12 years of age | do not use
adults 65 years of age and older | ask a doctor
consumers with kidney disease | ask a doctor

Other information

- store between 20-25ºC (68-77ºF)
- protect from excessive moisture

Inactive ingredients

colloidal silicon dioxide, croscarmellose sodium, hypromellose, iron oxide black, iron oxide red, iron oxide yellow, lactose monohydrate, pregelatinized starch, polyethylene glycol, magnesium stearate, microcrystalline cellulose, titanium dioxide

Questions or comments?

call 1-877-753-3935 Monday-Friday 9AM-5PM EST

Principal Display Panel

COMPARE TO THE ACTIVE INGREDIENT IN ALLEGRA® ALLERGY 24 HOUR*

ALLERGY RELIEF

Fexofenadine HCl Tablets USP, 180 mg

Antihistamine

24 HOUR RELIEF OF

- Runny nose
- Sneezing
- Itchy, watery eyes
- Itchy nose or throat

For indoor and outdoor allergies

Non-drowsy

CAPLETS**

(**CAPSULE-SHAPED TABLETS)

*This product is not manufactured or distributed by Sanofi Consumer Healthcare NA, distributor of Allegra® Allergy 24 Hour.

TAMPER EVIDENT: DO NOT USE IF PRINTED SAFETY SEAL UNDER CAP IS BROKEN OR MISSING.

KEEP OUTER CARTON FOR COMPLETE WARNINGS AND PRODUCT INFORMATION.

DISTRIBUTED BY

MIDWOOD BRANDS, LLC

510 VOLVO PARKWAY

CHESAPEAKE, VA 23320

Product Label

FAMILY WELLNESS Allergy Relief